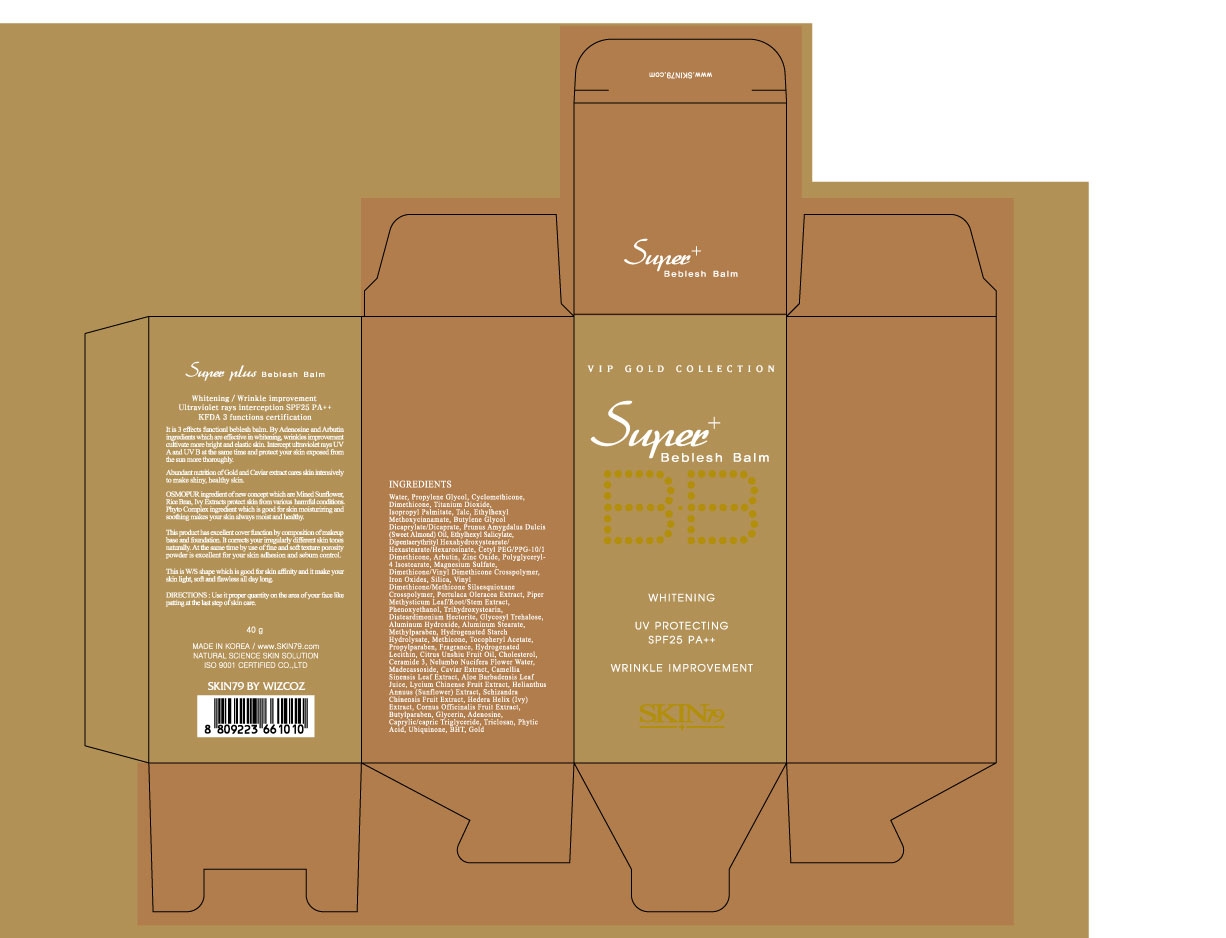 DRUG LABEL: SKIN 79 Super Plus Beblesh Balm SPF25 PA (40g)
NDC: 49715-002 | Form: CREAM
Manufacturer: WIZCOZ CORPORATION LTD
Category: otc | Type: HUMAN OTC DRUG LABEL
Date: 20091109

ACTIVE INGREDIENTS: TITANIUM DIOXIDE 1.92 g/40 g; ZINC OXIDE 0.78 g/40 g
INACTIVE INGREDIENTS: DIMETHICONE 2.2 g/40 g; ALUMINUM HYDROXIDE 0.072 g/40 g

ACTIVE INGREDIENT

INGREDIENTS:

Water, Propylene Glycol, Cyclomethicone, Dimethicone, Titanium Dioxide, Isopropyl Palmitate, Talc, Ethylhexyl Methoxycinnamate, Butylene Glycol, Dicaprylate/Dicaprate, Prunus Amygdalus Delcis (Sweet Almond) Oil, Ethylhexyl Salicylate, Digenlacrythrityl Hexahydroxystearate/Hexastearate/Hexarosinate, Cetyl PEG/PPG-10/1 Dimethicone, Arbulia, Zinc Oxide, Polyglyceryl-4 Isostearate, Magnesium Sulfate, Dimethicone[Vinyl] Dimethicone Crosspolymer, Iron Oxides, Silica, Vinyl Dimethicone/Methicone Silsesquioxane Crosspolymer, Portulaca Oleracea Extract, Piper Methyslicum Leaf/Root/Steam Extract, Phenoxyethanol, Trihydroxystearia, Disteardimonium Hectorite, Glycosyl Trichalose, Aluminum Hydroxide, Aluminum Stearate, Methylparaben, Hydrogenated Starch Hydrolysate, Methicone, Tocopheryl Acetate, Propylparaben, Fragrance, Hydrogenated Lecithin, Citrus Umshiu Fruit Oil, Cholesterol, Ceramide 3, Nelumbo Nucifera Flower Water, Medocassoside, Caviar Extract, Camellia Sipcasis Leaf Extract, Aloe Barbedensis Leaf Juice, Lycium Chinenese Fruit Extract, Hellanthus Annus (Sun Flower) Extract, Schizandra Chinensis Fruit Extract, Hedera Helix (Ivy) Extract, Cornus Officixalis Fruit Extract, Bubylparaben, Glycerin, Adenosine, Caprylic/capric Triglyceride, Triclosan, Phytic Acid, Ubiquinose, BHT, Gold

WHEN USING

DIRECTIONS: Use it proper quantity on the area of your face like patting at the last step of skin care.